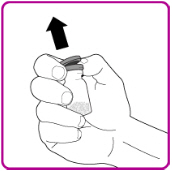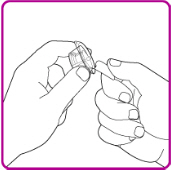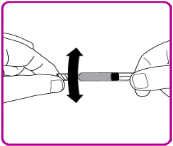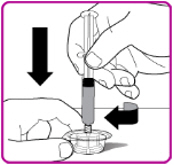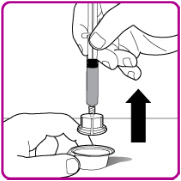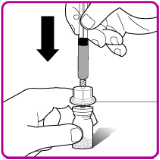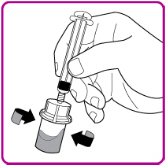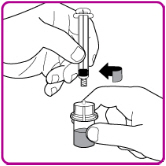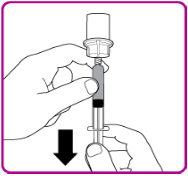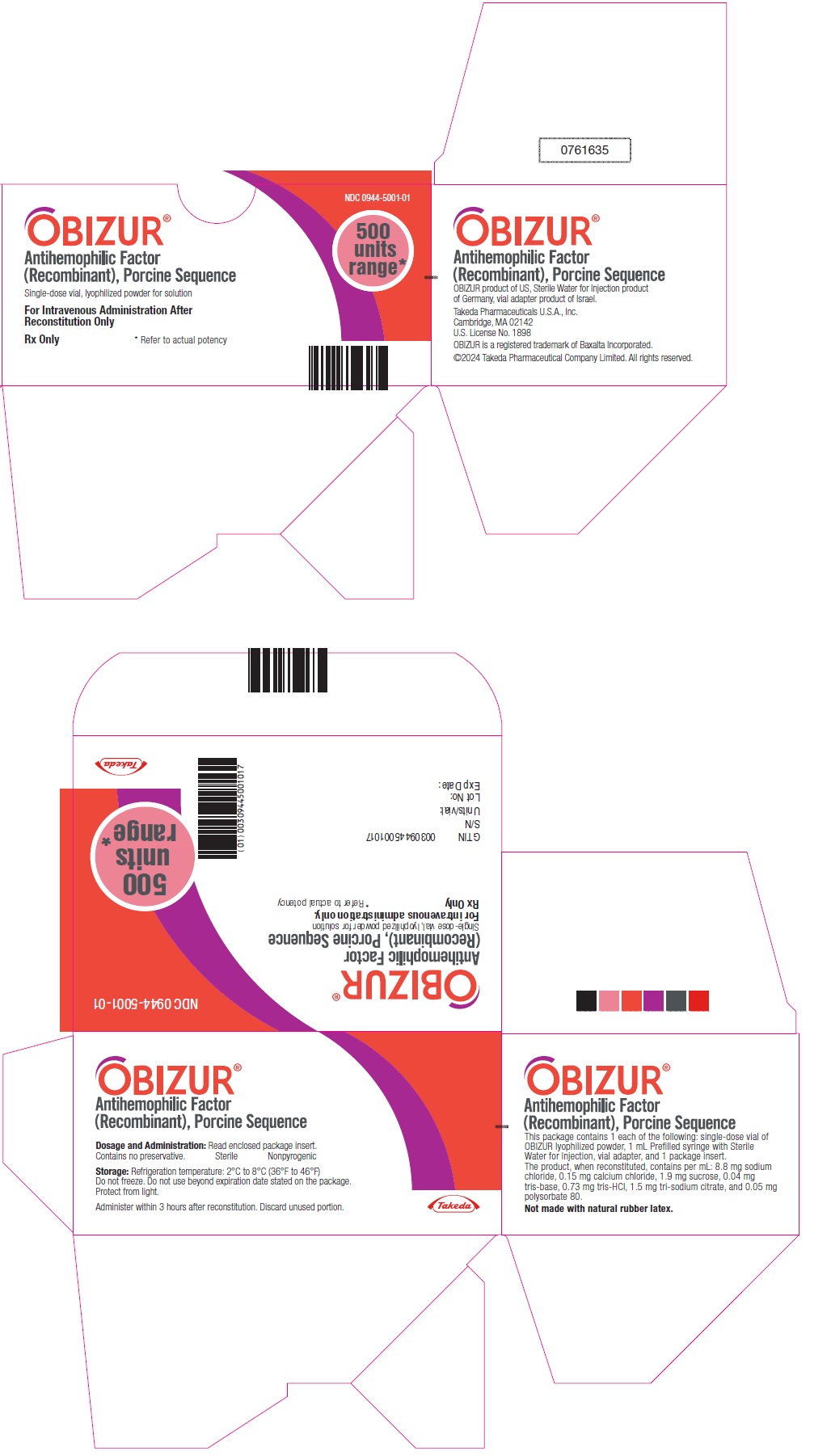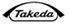 DRUG LABEL: OBIZUR
NDC: 0944-5001 | Form: KIT | Route: INTRAVENOUS
Manufacturer: Takeda Pharmaceuticals America, Inc.
Category: other | Type: PLASMA DERIVATIVE
Date: 20250305

ACTIVE INGREDIENTS: SUSOCTOCOG ALFA 500 [USP'U]/1 mL
INACTIVE INGREDIENTS: SODIUM CHLORIDE; CALCIUM CHLORIDE; SUCROSE; TROMETHAMINE; TROMETHAMINE HYDROCHLORIDE; SODIUM CITRATE, UNSPECIFIED FORM; POLYSORBATE 80; WATER 1 mL/1 mL

HIGHLIGHTS OF PRESCRIBING INFORMATION

These highlights do not include all the information needed to use OBIZUR® safely and effectively. See full prescribing information for OBIZUR.
OBIZUR® [Antihemophilic Factor (Recombinant), Porcine Sequence]
Lyophilized Powder for Solution for Intravenous Injection
Initial U.S. Approval: 2014

1 INDICATIONS AND USAGE

OBIZUR, Antihemophilic Factor (Recombinant), Porcine Sequence, is an antihemophilic factor indicated for the on-demand treatment and control of bleeding episodes in adults with acquired hemophilia A. (1)

Limitations of Use:

- Safety and efficacy of OBIZUR has not been established in patients with a baseline anti-porcine factor VIII inhibitor titer of greater than 20 BU. (1)
- OBIZUR is not indicated for the treatment of von Willebrand disease. (1)

2 DOSAGE AND ADMINISTRATION

For intravenous use after reconstitution only.

- Initial dose of OBIZUR is 200 units per kg. (2.1)
- Titrate dose and frequency of administration based on factor VIII recovery levels and individual clinical response. (2.1)
- Initial dosing below the recommended 200 U/kg has been associated with lack of efficacy. (2.1)

3 DOSAGE FORMS AND STRENGTHS

OBIZUR is available as lyophilized powder for solution in single-dose vials containing nominally 500 units per vial. (3)

4 CONTRAINDICATIONS

- Patients who have had life-threatening hypersensitivity reactions to OBIZUR or its components, including hamster protein. (4)
- Patients with congenital hemophilia A with inhibitors (4)

5 WARNINGS AND PRECAUTIONS

- Hypersensitivity reactions, including anaphylaxis, may occur. Should symptoms occur, discontinue OBIZUR and administer appropriate treatment. (5.1)
- Development of inhibitory antibodies to OBIZUR has occurred and may result in a lack of efficacy. (5.2)
- Anamnestic reactions with rise in human factor VIII and/or recombinant factor VIII, porcine sequence inhibitors have occurred and may result in a lack of efficacy. (5.2)
- Consider evaluating for presence of anti-recombinant porcine factor VIII (anti-rpFVIII) antibodies prior to initiation of treatment with OBIZUR. If expected plasma factor VIII activity levels are not attained, or if bleeding is not controlled with an appropriate dose, perform an assay that measures porcine factor VIII inhibitor concentration. In instances where positive anti-rpFVIII antibody results are detected after treatment with OBIZUR is initiated, factor VIII levels may be used to decide whether treatment with OBIZUR should be continued. (5.2) (5.3)

6 ADVERSE REACTIONS

Common adverse reaction observed in greater than 5% of subjects in the clinical trial were development of inhibitors to porcine factor VIII. (6.1)

To report SUSPECTED ADVERSE REACTIONS, contact Takeda Pharmaceuticals U.S.A., Inc. at 1-877-TAKEDA-7 (1-877-825-3327) or FDA at 1-800-FDA-1088 or www.fda.gov/medwatch.

FULL PRESCRIBING INFORMATION

1 INDICATIONS AND USAGE

OBIZUR®, Antihemophilic Factor (Recombinant), Porcine Sequence, is a recombinant DNA derived, antihemophilic factor indicated for the on-demand treatment and control of bleeding episodes in adults with acquired hemophilia A.

Limitations of Use:

- Safety and efficacy of OBIZUR has not been established in patients with baseline anti-porcine factor VIII inhibitor titer greater than 20 BU.
- OBIZUR is not indicated for the treatment of von Willebrand disease.

2 DOSAGE AND ADMINISTRATION

For intravenous use after reconstitution only.

2.1 Dose

- Dose, dosing frequency, and duration of treatment with OBIZUR depend on the location and severity of bleeding episode, target factor VIII levels, and the patient's clinical condition. Monitor replacement therapy in cases of major surgery or life-threatening bleeding episodes.
- Each vial of OBIZUR has the recombinant porcine factor VIII potency in units stated on the vial.
- Patients may vary in their pharmacokinetic (e.g., half-life, in vivo recovery) and clinical responses. Titrate dose and frequency based on factor VIII recovery levels and individual clinical response.
- Initial dosing below the recommended 200 U/kg has been associated with lack of efficacy.

A guide for dosing OBIZUR for the on-demand treatment and control of bleeding episodes is provided in Table 1. Maintain the factor VIII activity within the target range. Plasma levels of factor VIII should not exceed 200% of normal or 200 units per dL.

Table 1 Dosing for On-Demand Treatment and Control of Bleeding Episodes
Type of Bleeding | Factor VIII Level Required (Units per dL or % of normal) | Initial Dose (Units per kg) | Subsequent Dose | Frequency and Duration of Subsequent Dosing
Minor and Moderate Superficial muscle/no neurovascular compromise, and joint | 50 to 100 | 200 | Titrate subsequent doses to maintain recommended factor VIII trough levels and individual clinical response | Dose every 4 to 12 hours, frequency may be adjusted based on clinical response and measured factor VIII levels
Major Moderate to severe intramuscular bleeding, retroperitoneal, gastrointestinal, intracranial | 100 to 200 (To treat an acute bleed) 50 to 100 (After acute bleed is controlled, if required) | 200 | Titrate subsequent doses to maintain recommended factor VIII trough levels and individual clinical response | Dose every 4 to 12 hours, frequency may be adjusted based on clinical response and measured factor VIII levels

2.2 Reconstitution

- Use aseptic technique during the reconstitution procedure.
- If the patient needs more than one vial of OBIZUR per injection, reconstitute each vial according to the following instructions:

1. Bring the OBIZUR vial and the pre-filled diluent syringe to room temperature.
2. Remove the plastic cap from the OBIZUR vial (Figure A).

Figure A

3. Wipe the rubber stopper with an alcohol swab (not supplied) and allow it to dry prior to use.
4. Peel back the cover of the vial adapter package. (Figure B). Do not touch the luer-lock (tip) in the center of the vial adapter. Do not remove the vial adapter from the plastic package.

Figure B

5. Place the vial adapter package on a clean surface with the luer-lock pointing up.
6. Snap off the tamper resistant cap of the pre-filled syringe (Figure C).

Figure C

7. While firmly holding the vial adapter package, connect the pre-filled syringe to the vial adapter by pushing the syringe tip down onto the luer lock in the center of the vial adapter, and turning it clockwise until the syringe is secured. Do not over tighten (Figure D).

Figure D

8. Remove the vial adapter from the plastic package (Figure E).

Figure E

9. Place the OBIZUR vial on a clean, flat, hard surface. Place the vial adapter over the OBIZUR vial and firmly push the filter spike of the vial adapter through the center of the OBIZUR vial's rubber circle until the clear plastic cap snaps onto the vial (Figure F).

Figure F

10. Push the plunger down to slowly inject all of the diluent from the syringe into the OBIZUR vial.
11. Gently swirl (in a circular motion) the OBIZUR vial without removing the syringe until all of the powder is fully dissolved (Figure G). The reconstituted solution should be inspected visually for particulate matter before administration. Do not use if particulate matter or discoloration is observed.

Figure G

12. With one hand hold the vial and vial adapter, and with the other hand firmly grasp the barrel of the pre-filled syringe and in a counterclockwise motion unscrew the syringe from the vial adapter (Figure H).

Figure H

13. Use OBIZUR within 3 hours after reconstitution when stored at room temperature.

2.3 Administration

For intravenous use after reconstitution only.

- Inspect the reconstituted OBIZUR solution for particulate matter and discoloration prior to administration. The solution should be clear and colorless in appearance. Do not administer if particulate matter or discoloration is observed.
- Do not administer OBIZUR in the same tubing or container with other medicinal products for infusion.

1. Once all vials have been reconstituted, connect a large syringe to the vial adapter by gently pushing the syringe tip down onto the luer lock in the center of the vial adapter, and turning clockwise until the syringe is secured.
2. Invert the vial; push the air in the syringe into the vial and withdraw the reconstituted OBIZUR into the syringe (Figure I).

Figure I

3. Unscrew the large syringe counterclockwise from the vial adapter and repeat this process for all reconstituted vials of OBIZUR until the total volume to be administered is reached.
4. Administer the reconstituted OBIZUR intravenously at a rate of 1 to 2 mL per minute.

3 DOSAGE FORMS AND STRENGTHS

OBIZUR is available as a white lyophilized powder in single-dose glass vials containing nominally 500 units per vial.

4 CONTRAINDICATIONS

OBIZUR is contraindicated in patients:

- Who have had life-threatening hypersensitivity reactions to OBIZUR or its components (including traces of hamster proteins).
- With congenital hemophilia A with inhibitors (CHAWI) due to the high incidence of anamnestic reactions to human factor VIII (hFVIII) and porcine factor VIII (pFVIII) [see Adverse Reactions (6.1)].

5 WARNINGS AND PRECAUTIONS

5.1 Hypersensitivity Reactions

Hypersensitivity reactions can occur with OBIZUR. OBIZUR contains trace amounts of hamster proteins. Early signs of allergic reactions, which can progress to anaphylaxis, include angioedema, chest-tightness, dyspnea, hypotension, wheezing, urticaria, and pruritus. Immediately discontinue administration and initiate appropriate treatment if allergic or anaphylactic-type reactions occur.

5.2 Inhibitory Antibodies

Inhibitory antibodies to OBIZUR have occurred in patients treated with OBIZUR. Lack of efficacy could be due to inhibitory antibodies to OBIZUR.

Anamnestic reactions with rise in human factor VIII and/or recombinant factor VIII, porcine sequence inhibitors have also been reported in patients treated with OBIZUR. These anamnestic rises also may result in lack of efficacy.

Consider evaluating for presence of anti-recombinant porcine factor VIII (anti-rpFVIII) antibodies prior to initiation of treatment with OBIZUR. In instances where positive anti-rpFVIII antibody results are detected after treatment with OBIZUR is initiated, factor VIII levels may be used to decide whether treatment with OBIZUR should be continued [see Warnings and Precautions (5.3)].

Monitor patients for the development of antibodies to OBIZUR by appropriate assays [see Warnings and Precautions (5.3)]. If the plasma factor VIII level fails to increase as expected, or if bleeding is not controlled after OBIZUR administration, suspect the presence of an anti-porcine factor VIII antibody.

If such inhibitory antibodies are suspected and there is a lack of efficacy, consider management options such as discontinuing OBIZUR and initiating other therapeutics such as a Factor VIII bypassing agent.

5.3 Monitoring Laboratory Tests

- Perform one-stage clotting assay to confirm that adequate factor VIII levels have been achieved and maintained [see Dosage and Administration (2)].
  - Monitor factor VIII activity 30 minutes and 3 hours after initial dose.
  - Monitor factor VIII activity 30 minutes after subsequent doses.
- Monitor the development of inhibitory antibodies to OBIZUR. Perform a Nijmegen Bethesda inhibitor assay with recombinant porcine factor VIII as substrate for recombinant porcine factor VIII antibodies if expected plasma factor VIII activity levels are not attained or if bleeding is not controlled with the expected dose of OBIZUR. Use Bethesda Units (BU) to report inhibitor levels. Contact Takeda Pharmaceuticals U.S.A., Inc. at 1-877-TAKEDA-7 (1-877-825-3327) if additional information is needed regarding testing.

6 ADVERSE REACTIONS

Common adverse reactions observed in greater than 5% of subjects in the clinical trial were development of inhibitors to porcine factor VIII.

6.1 Clinical Trials Experience

Because clinical trials are conducted under widely varying conditions, adverse reaction (AR) rates observed in the clinical trials of a drug cannot be directly compared to rates in the clinical trials of another drug and may not reflect the rates observed in clinical practice.

The safety and efficacy of OBIZUR was evaluated in a multi-center, prospective, open-label, clinical trial that investigated adult patients with acquired hemophilia A. Twenty-nine adult subjects were enrolled in the study, received at least one dose of OBIZUR and were evaluable for safety [see Clinical Studies (14)]. Of the 29 adult subjects, 10 were between the ages of 42 and 65, and 19 were 65 years of age or older (18 Caucasian, 6 African-American, and 5 Asian). Ten (34%) subjects were female.

Immunogenicity: Anti-Drug Antibody-Associated Adverse Reactions

All subjects were monitored for development of inhibitory antibodies to OBIZUR using the Nijmegen modification of the Bethesda inhibitor assay. A subject was considered to have developed an OBIZUR inhibitor if the titer was ≥0.6 Bethesda Units (BU)/mL.

Acquired Hemophilia A

Of the 29 subjects treated with OBIZUR, 19 subjects were negative for anti-porcine factor VIII antibodies at baseline. Five of the 19 (26%) developed anti-porcine factor VIII antibodies following exposure to OBIZUR. Serious adverse drug reactions (ADRs) occurred in 9 subjects. Two subjects (6.9%) developed anti-porcine FVIII inhibitors (≥0.6 Bethesda Units). Seven subjects (24.1%) developed anamnestic reactions with a rise ≥10 BU in human factor VIII and/or recombinant factor VIII, porcine sequence inhibitors. At 24 hours after initial dose, OBIZUR was effective in 9/10 patients with baseline anti-porcine antibodies (and partially effective in 1/10 patients) and was effective in all 5 with de novo anti-porcine antibodies.

All subjects were also monitored for development of binding antibodies to baby hamster kidney (BHK) protein by a validated sequential ELISA (enzyme-linked immunosorbent assay). No patients developed de novo anti-BHK antibodies.

The detection of antibody formation is highly dependent on the sensitivity and specificity of the assay. Additionally, the observed incidence of antibody (including neutralizing antibody) positivity in an assay may be influenced by several factors, including assay methodology, sample handling, timing of sample collection, concomitant medications, and underlying disease. For these reasons, comparison of the incidence of antibodies to OBIZUR with the incidence of antibodies to other products may be misleading.

Congenital Hemophilia A with Inhibitors

In the clinical study of OBIZUR in patients with congenital hemophilia A with FVIII inhibitors (CHAWI) undergoing surgery, out of 8 adult patients evaluable for safety analysis a total of 5 subjects experienced anamnestic reactions [see Contraindications (4)].

A total of 5 (62.5%) subjects who underwent major surgeries reported anamnestic reactions with a rise ≥10 BU in human factor VIII and/or recombinant factor VIII, porcine sequence inhibitors (see Table 2). 3 (37.5%) subjects developed anamnestic reactions to human Factor VIII (hFVIII) and porcine Factor VIII (pFVIII), 2 (25.0%) subjects developed anamnestic reactions to hFVIII. The highest increases in antibody levels reported are from 15.4 at baseline to 1039.6 BU for hFVIII and from 2.6 to 335.8 BU for pFVIII. Inhibitory antibodies may result in lack of efficacy.

Table 2 Titer Levels of Subjects Experiencing Anamnestic Reactions
Subjects | hFVIII Inhibitors Titers (BU/mL) |  |  | Obizur pFVIII Inhibitors Titers (BU/mL)
Subjects | Baseline | Day 14 Visit | End of the Study Visit | Baseline | Day 14 Visit | End of the Study Visit
Subject 1 | 1.3 | 1.2 (D3) | 38.1/39.9 | <0.6 | <0.6 (D3) | 29.3/38.8
Subject 2 | 15.4 |  | 1039.6 /807.9 | 2.6 | 0.7 (D5) | 327.3/335.8
Subject 3 | 3.3 | 19.9 (D20) | 23.3 | 5.6 | 36.1 (D20) | 30.5
Subject 4 | 2.6 | 16.6 | 12.1 | <0.6 | 1 | 0.9
Subject 5 | 4.6 | 3.8 (D3)/488 (D16) | 336.3 | 1.7 | <0.6 (D3)/285.9 (D16) | 280.5

8 USE IN SPECIFIC POPULATIONS

8.1 Pregnancy

Risk Summary

There are no data with OBIZUR use in pregnant women to inform a drug-associated risk. There are no adequate and well-controlled studies in pregnant women. Animal reproduction studies have not been conducted with OBIZUR. It is also not known whether OBIZUR can cause fetal harm when administered to a pregnant woman or can affect reproduction capacity.

In the U.S. general population, the estimated background risk for major birth defects and miscarriage in clinically recognized pregnancies is 2 to 4% and 15 to 20%, respectively.

8.2 Lactation

Risk Summary

There is no information regarding the presence of OBIZUR in human milk, the effect on the breastfed child, or the effects on milk production.

The developmental and health benefits of breastfeeding should be considered along with the mother's clinical need for OBIZUR and any potential adverse effects on the breastfed child from OBIZUR or from the underlying maternal condition.

8.4 Pediatric Use

The safety and efficacy of OBIZUR have not been established in pediatric patients.

8.5 Geriatric Use

Of the 29 subjects within the trial, the average age was 70 years of age. Nineteen subjects were 65 years of age or older. Clinical studies suggest that OBIZUR is safe and effective in the adult population [see Adverse Reactions (6) and Clinical Studies (14)]. While no differences were observed between geriatric and adult responses to OBIZUR, these findings are inconclusive given the small number of subjects enrolled in either group.

Dose adjustments in the geriatric population have not been studied. Specific hazards associated with the concomitant use of OBIZUR with other drugs in the elderly population have not been studied in the clinical trial.

11 DESCRIPTION

The active ingredient in OBIZUR is a recombinant (r) analogue of porcine factor VIII (pFVIII) with an approximate molecular weight of 170 kDa. The rpFVIII molecule in OBIZUR is a glycoprotein containing a 90 kDa heavy chain and a 80 kDa light chain. The B-domain normally present in naturally occurring porcine factor VIII has been replaced with a twenty-four amino acid linker. Once activated, the resulting rpFVIIIa has a comparable activity to the endogenous human FVIIIa.

OBIZUR is expressed in a genetically engineered baby hamster kidney (BHK) cell line which secretes rpFVIII into the cell culture medium, and the rpFVIII protein is purified using a series of chromatography and filtration steps. The production process includes two dedicated viral clearance steps - a solvent/detergent treatment step for viral inactivation and a nanofiltration step through a series of two 15-nm filters for removal of viruses. No additives of human or animal origin are used in the formulation of OBIZUR.

OBIZUR is formulated as a sterile, non-pyrogenic, lyophilized powder for intravenous injection after reconstitution with the diluent (Sterile Water for Injection). OBIZUR is available in single-dose vials that nominally contain 500 units (U) per vial. When reconstituted with the diluent, the product contains the following components per mL: 8.8 mg sodium chloride, 0.04 mg Tris-base, 0.73 mg Tris-HCl, 1.47 mg tri-sodium citrate dehydrate, 0.15 mg calcium chloride dehydrate, 1.9 mg sucrose, and 0.05 mg polysorbate 80.

Each vial of OBIZUR is labeled with the actual rpFVIII activity expressed in units determined by a one-stage clotting assay, using a reference rpFVIII material calibrated against the World Health Organization (WHO) 8th International Standard for human FVIII concentrates. The specific activity of OBIZUR is in the range of 11000 to 18000 U per milligram of protein. The potency values of OBIZUR determined by the chromogenic assay vary and are approximately 20 to 50% lower than those of the one-stage clotting assay.

12 CLINICAL PHARMACOLOGY

12.1 Mechanism of Action

OBIZUR temporarily replaces the inhibited endogenous factor VIII that is needed for effective hemostasis in patients with acquired hemophilia A.

12.2 Pharmacodynamics

Patients with acquired hemophilia A (AHA) have normal factor VIII genes but develop autoantibodies against their own factor VIII (i.e., inhibitors). These autoantibodies neutralize circulating human factor VIII and create a functional deficiency of this procoagulant protein. AHA results in a prolonged clotting time as measured by the activated partial thromboplastin time (aPTT) assay, a conventional in vitro test for biological activity of factor VIII. Treatment with OBIZUR should normalize the aPTT during treatment; however, aPTT normalization should not be used as a measure of efficacy.

12.3 Pharmacokinetics

A formal pharmacokinetic study of OBIZUR in patients diagnosed with AHA has not been conducted. There are insufficient pharmacokinetic data in patients treated with OBIZUR.

13 NONCLINICAL TOXICOLOGY

13.1 Carcinogenesis, Mutagenesis, Impairment of Fertility

Long-term studies in animals to evaluate the carcinogenic potential of OBIZUR, or studies to determine genotoxicity and the effects of OBIZUR on fertility, have not been performed.

14 CLINICAL STUDIES

The efficacy of OBIZUR for the treatment of serious bleeding episodes in subjects with acquired hemophilia A was investigated in a prospective, open-label trial (N=29). The trial was conducted in 18 Caucasian, 6 African-American, and 5 Asian subjects diagnosed with acquired hemophilia A (AHA), having auto-immune inhibitory antibodies to human factor VIII, and experiencing serious bleeding episodes that required hospitalization. Subjects with a prior history of bleeding disorders other than AHA, anti-porcine factor VIII antibody titer >20 Bethesda Units (BU), or in whom the bleeding episode was judged likely to resolve on its own were excluded. One subject was considered evaluable at study entry; however, it was later determined that this subject did not have AHA, leaving 28 subjects evaluable for efficacy.

An initial dose of 200 units per kg OBIZUR was administered to subjects for the treatment of life- or limb-threatening initial bleeding episodes. Patients were treated with OBIZUR until resolution of bleeding or dosing was continued at the physician's discretion according to the clinical assessment. These bleeding episodes included 19 intramuscular or joint bleeding episodes, 4 post-surgical bleeding episodes, 2 intracranial episodes, 2 surgeries, 1 retroperitoneal hemorrhage, and 1 periorbital bleed. Hemostatic response was assessed by the study site investigator at specified time points after initiation of OBIZUR treatment using a pre-specified rating scale that was based on subjective clinical assessments combined with objective factor VIII activity levels achieved. An assessment of effective or partially effective was considered as a positive response (see Table 3 for definitions).

Table 3 Response to OBIZUR Treatment Evaluation
Assessment of efficacy | Control of bleeding | Clinical Assessment | Factor VIII levels | Response
Effective | bleeding stopped | clinical control | ≥50% | positive
Partially effective | bleeding reduced | clinical stabilization or improvement; or alternative reason for bleeding | ≥20% | positive
Poorly effective | bleeding slightly reduced or unchanged | not clinically stable | <50% | negative
Not effective | bleeding worsening | Clinically deteriorating | <20% | negative

Of the 28 subjects evaluable for efficacy, all subjects had a positive response to treatment for the initial bleeding episodes at 24 hours after dosing. A positive response was observed in 95% (19/20) of subjects evaluated at 8 hours and 100% (18/18) at 16 hours.

In addition to response to treatment, the overall treatment success was determined by the investigator based on his/her ability to discontinue or reduce the dose and/or dosing frequency of OBIZUR. A total of 24/28 (86%) had successful treatment of the initial bleeding episode. Of those subjects treated with OBIZUR as first-line therapy, defined as no immediate previous use of anti-hemorrhagic agents prior to the first OBIZUR treatment, 16/17 (94%) had eventual treatment success reported. Eleven subjects were reported to have received anti-hemorrhagics (e.g., rFVIIa, activated prothrombin-complex concentrate, tranexamic acid) prior to first treatment with OBIZUR. Of these 11 subjects, eight had eventual successful treatment (73%).

The median dose per infusion to successfully treat the primary bleeding episode was 133 units per kg and a median total dose of 1523 units per kg. In the initial 24-hour period, a median of 3 infusions (median dose 200 U/kg) were utilized in the clinical study. When treatment was required beyond 24 hours, a median of 10.5 infusions (median dose 100 U/kg) were given for a median of 6 days to control a bleeding episode.

16 HOW SUPPLIED/STORAGE AND HANDLING

How Supplied

OBIZUR is supplied as a white lyophilized powder in single-dose vials in the following package size:

Table 4 Supplied package size
Nominal Strength | Package Size | Kit NDC
500 units | 1-vial package | 0944-5001-01

Each package contains one package insert and one of each of the components listed below:

- Single-dose vial of OBIZUR [NDC 0944-5011-01]
- Pre-filled syringe with 1 mL Sterile Water for Injection [NDC 0944-0011-01]
- Vial adapter with filter

The actual amount of OBIZUR in units is stated on the label of each vial.

Not made with natural rubber latex.

Storage and Handling

- Store OBIZUR at refrigeration temperature of 2° to 8°C [36° to 46°F]. Do not freeze.
- Store vials in the original package to protect from light.
- Do not use beyond the expiration date printed on the carton or vial.
- Use OBIZUR within 3 hours after reconstitution. Discard any unused reconstituted product if not used within 3 hours after reconstitution.
- Do not use OBIZUR if the reconstituted solution is cloudy or has particulate matter.

17 PATIENT COUNSELING INFORMATION

Inform patients:

- of early signs and symptoms of hypersensitivity reactions (including angioedema, chest tightness, dyspnea, hypotension, wheezing, urticaria and pruritus) and anaphylaxis. Instruct patients to discontinue use and contact their physician.
- that new or increase in existing inhibitory antibodies to OBIZUR may develop and this may result in a lack of control of their bleeding.
- to report any adverse reactions or problems following OBIZUR administration to their physician or healthcare provider.

Takeda Pharmaceuticals U.S.A., Inc.
Cambridge, MA 02142 USA
U.S. License No. 1898

OBIZUR is a registered trademark of Baxalta Incorporated.
Takeda and are registered trademarks of Takeda Pharmaceutical Company Limited.

©2024 Takeda Pharmaceutical Company Limited. All rights reserved.

OBZ363 Rev 12/2024

PRINCIPAL DISPLAY PANEL - Kit Carton

NDC 0944-5001-01

OBIZUR®
Antihemophilic Factor
(Recombinant), Porcine Sequence

Single-dose vial, lyophilized powder for solution

For Intravenous Administration After
Reconstitution Only

500
units
range*

Rx Only
* Refer to actual potency